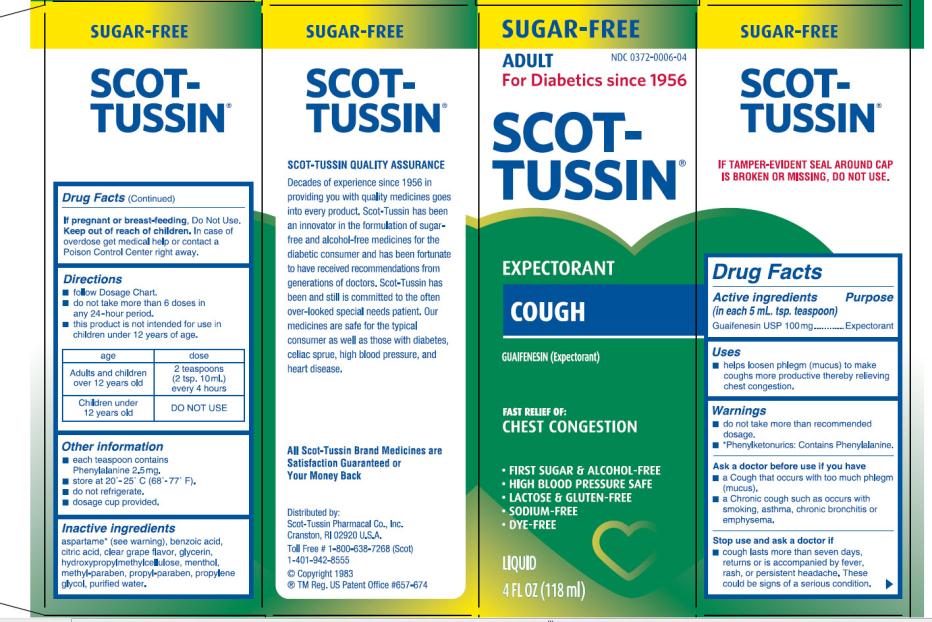 DRUG LABEL: Scot-Tussin Expectorant SF Cough
NDC: 0372-0006 | Form: LIQUID
Manufacturer: SCOT-TUSSIN Pharmacal Co., Inc.
Category: otc | Type: HUMAN OTC DRUG LABEL
Date: 20130129

ACTIVE INGREDIENTS: GUAIFENESIN 100 mg/5 mL
INACTIVE INGREDIENTS: ASPARTAME; BENZOIC ACID; CITRIC ACID MONOHYDRATE; GLYCERIN; HYPROMELLOSES; MENTHOL; METHYLPARABEN; PROPYLPARABEN; PROPYLENE GLYCOL; WATER

Scot-Tussin Expectorant SF Cough

Active Ingredient:

(in each 5 mL. tsp. teaspoon)

Guaifenesin 100mg

Purpose

Expectorant

Uses

- Helps loosen phlegm (mucus) to make coughs more productive thereby relieving chest congestion.

Warnings

- Do not exceed recommended dosage.
- *Phenylketonurics: Contains Phenylalanine.

When using this product

- Don’t take more than the recommended dosage.

Ask a doctor before use if you have

- a Cough that occurs with too much phlegm (mucus).
- a Chronic cough such as occurs with smoking, asthma, chronic bronchitis or emphysema.

Stop use and ask a doctor if

- Cough lasts more than seven days, returns or is accompanied by fever, rash, or persistent headache. These could be signs of a serious condition.

If pregnant or breast-feeding,

Do Not Use.

Keep out of reach of children.

In case of overdose get medical help or contact a Poison Control Center right away.

Directions:

- Follow Dosage Chart.
- Do not take more than the six doses in any 24 hour period.
- This product is not intended for use in children under 12 years of age.

age | dose
Adults and children over 12 years old | 2 teaspoons (2 tsp. 10 ml) every 4 hours
Children Under 12 years old | DO NOT USE

Other Information

- each teaspoon contains Phenylalanine 2.5 mg
- store at 20º – 25º C (68º – 77º F).
- do not refigerate.
- dosage cup provided.

Inactive Ingredients

Aspartame* (see warning) Benzoic Acid, Citric Acid, Clear Grape Flavor, Glycerin, Hydroxypropylmethylcellulose, Menthol, Methyl Paraben, Propyl Paraben, Propylene Glycol, Purified Water.

PRINCIPAL DISPLAY PANEL

NDC 0372-0006-04

SCOT-TUSSIN

EXPECTORANT

COUGH

4 FL OZ (118 ml)